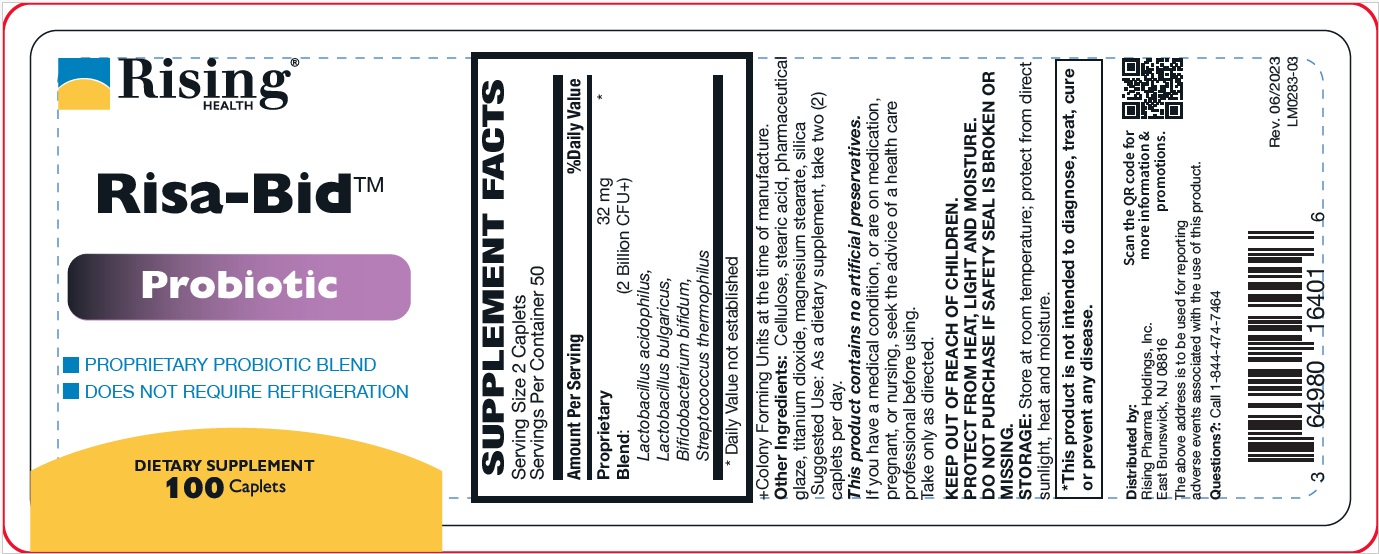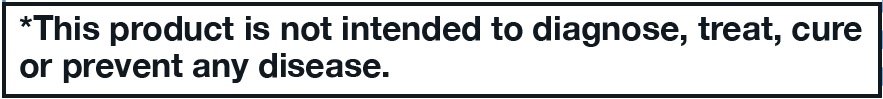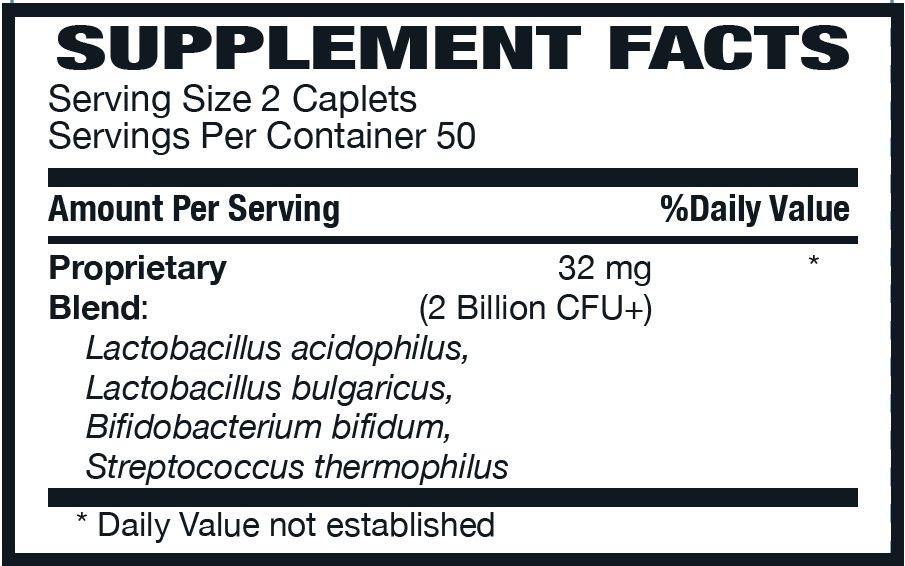 DRUG LABEL: Risa-Bid Caplet
NDC: 64980-164 | Form: TABLET
Manufacturer: Rising Pharma Holdings, Inc.
Category: other | Type: DIETARY SUPPLEMENT
Date: 20250610

ACTIVE INGREDIENTS: LACTOBACILLUS ACIDOPHILUS 2000000000 [CFU]/1 1; LACTOBACILLUS DELBRUECKII BULGARICUS 2000000000 [CFU]/1 1; BIFIDOBACTERIUM BIFIDUM 2000000000 [CFU]/1 1; STREPTOCOCCUS THERMOPHILUS 2000000000 [CFU]/1 1
INACTIVE INGREDIENTS: POWDERED CELLULOSE; STEARIC ACID; SHELLAC; TITANIUM DIOXIDE; MAGNESIUM STEARATE; SILICA

Risa-BidTM, 100 Caplets, Dietary Supplement

HEALTH CLAIM

+Colony Forming Units at the time of manufacture.

Other Ingredients: Cellulose, stearic acid, pharmaceutical glaze, titanium dioxide, magnesium stearate, silica

DOSAGE AND ADMINISTRATION

Suggested Use: As a dietary supplement, take two (2) caplets per day.

This product contains no artificial preservatives.

WARNINGS

If you have a medical condition, or are on medication, pregnant, or nursing, seek the advice of a health care professional before using.

Take only as directed.

KEEP OUT OF REACH OF CHILDREN.

PROTECT FROM HEAT, LIGHT AND MOISTURE.

DO NOT PURCHASE IF SAFETY SEAL IS BROKEN OR MISSING.

STORAGE: Store at room temperature; protect from direct sunlight, heat and moisture.

Distributed by:

Rising Pharma Holdings, Inc.
East Brunswick, NJ 08816

The above address is to be used for reporting adverse events associated with the use of this product.

Questions?:Call 1-844-474-7464

Rev. 06/2023

LM0283-03

PACKAGE LABEL.PRINCIPAL DISPLAY PANEL

Risa-BidTM

Probiotic

DIETARY SUPPLEMENT

100 Caplets

Bottle Label (64980-164-01)